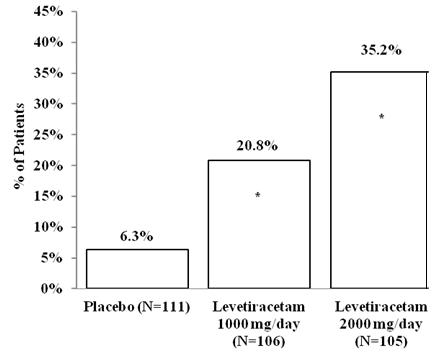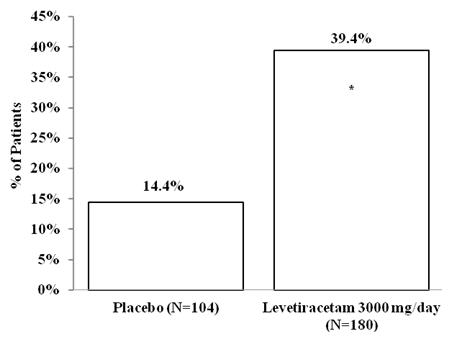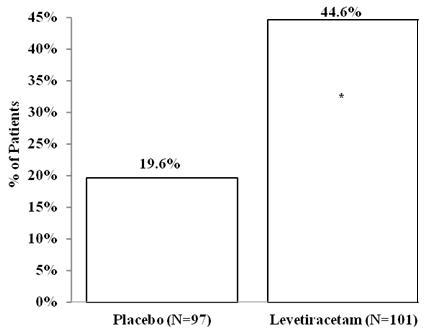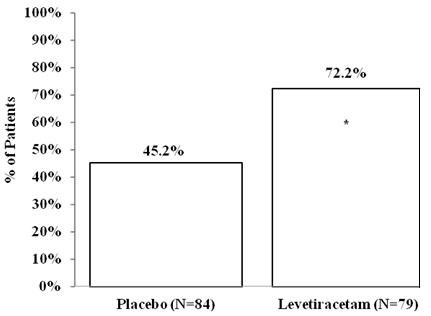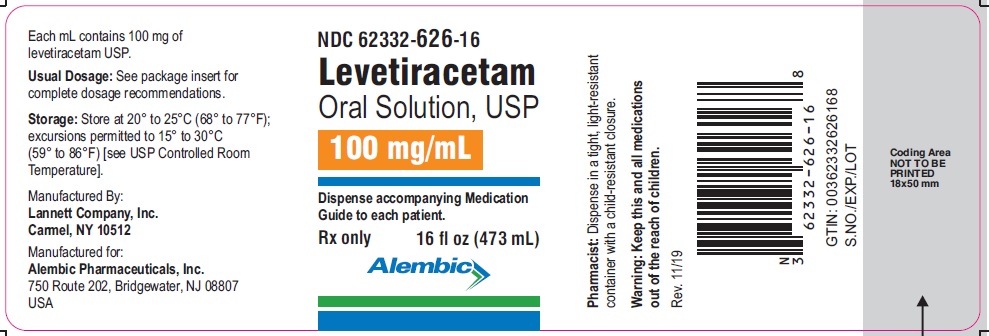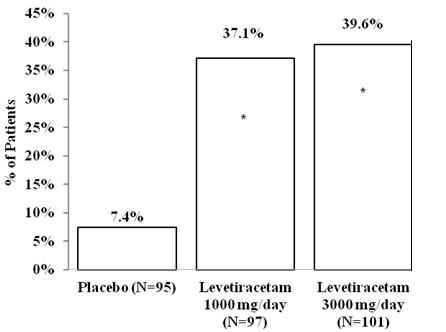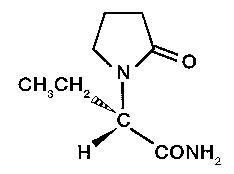 DRUG LABEL: LEVETIRACETAM
NDC: 62332-626 | Form: SOLUTION
Manufacturer: Alembic Pharmaceuticals Inc.
Category: prescription | Type: Human Prescription Drug Label
Date: 20191113

ACTIVE INGREDIENTS: LEVETIRACETAM 100 mg/1 mL
INACTIVE INGREDIENTS: ACESULFAME POTASSIUM; ANHYDROUS CITRIC ACID; GLYCERIN; MALTITOL; METHYLPARABEN; AMMONIUM GLYCYRRHIZATE; PROPYLPARABEN; WATER; SODIUM CITRATE

HIGHLIGHTS OF PRESCRIBING INFORMATION

These highlights do not include all the information needed to use Levetiracetam Oral Solution, USP safely and effectively. See full prescribing information for Levetiracetam Oral Solution, USP.
Levetiracetam Oral Solution, USP
Initial U.S. Approval: 1999

RECENT MAJOR CHANGES

I n d ic a t io ns a nd Us a g e, P a r t i al O ns et S ei z u r es (1 . 1) [ 1 2 / 20 11]

D os a ge a nd A d m i n is t r a t io n, P a r t i al O ns et S e i z u r es (2 . 1, 2 . 2, 2 . 5) [1 2 /2 0 1 1]
W a r n in gs a nd Pr e c a u t i o ns (5 . 1, 5 . 3, 5 . 4, 5 . 5, 5 . 7, 5 . 8, 5 . 9) [ 1 2 / 20 1 1]

1 INDICATIONS AND USAGE

Levetiracetam Oral Solution, USP is an antiepileptic drug indicated for adjunctive therapy in the treatment of:
• Partial onset seizures in patients 4 years of age and older with epilepsy (1.1)
• Myoclonic seizures in patients 12 years of age and older with juvenile myoclonic epilepsy (1.2)
• Primary generalized tonic-clonic seizures in patients 6 years of age and older with idiopathic generalized epilepsy (1.3)

2 DOSAGE AND ADMINISTRATION

• Use the oral solution for pediatric patients with body weight ≤ 20 kg (2.1).
• For pediatric patients, use weight-based dosing for the oral solution with a calibrated measuring device (not a household teaspoon or tablespoon) (2.1)

Partial Onset Seizures
• 4 Years To < 16 Years: 10 mg/kg twice daily, increase in increments of 10
mg/kg twice daily every 2 weeks to recommended dose of 30 mg/kg twice daily (2.2)
• Adults 16 Years And Older: 500 mg twice daily, increase as needed and tolerated in increments of 500 mg twice daily every 2 weeks to a maximum recommended dose of 1500 mg twice daily (2.2)

Myoclonic Seizures In Adults and Pediatric Patients 12 Years And Older
• 500 mg twice daily, increase by 500 mg twice daily every 2 weeks to recommended dose of 1500 mg twice daily (2.3)

Primary Generalized Tonic-Clonic Seizures
• 6 Years To < 16 Years: 10 mg/kg twice daily, increase in increments of 10 mg/kg twice daily every 2 weeks to recommended dose of 30 mg/kg twice daily (2.4)
• Adults 16 Years And Older: 500 mg twice daily, increase by 500 mg twice daily every 2 weeks to recommended dose of 1500 mg twice daily (2.4)
Adult patients with impaired renal function
• Dose adjustment is recommended, based on the patient's estimated creatinine clearance (2.5, 8.6)

3 DOSAGE FORMS AND STRENGTHS

• 100 mg/mL solution (3)

4 CONTRAINDICATIONS

• None (4)

5 WARNINGS AND PRECAUTIONS

• Psychiatric Symptoms: Behavioral abnormalities including psychotic symptoms, suicidal ideation, irritability, and aggressive behavior have been observed. Monitor patients for psychiatric signs and symptoms (5.1)
• Suicidal Behavior and Ideation: Monitor patients for new or worsening depression, suicidal thoughts/behavior, and/or unusual changes in mood or behavior (5.2)
• Somnolence and Fatigue: Monitor patients for these symptoms and advise patients not to drive or operate machinery until they have gained sufficient experience on levetiracetam (5.3)
• Withdrawal Seizures: Levetiracetam must be gradually withdrawn (5.6)

6 ADVERSE REACTIONS

Most common adverse reactions (incidence in levetiracetam-treated patients is ≥ 5% more than in placebo-treated patients) include:
• Adult patients: somnolence, asthenia, infection and dizziness (6.1)
• Pediatric patients: fatigue, aggression, nasal congestion, decreased appetite, and irritability (6.1)

To report SUSPECTED ADVERSE REACTIONS, contact Silarx Pharmaceuticals, Inc. at 1-888-974-5279 or FDA at 1-800-FDA-1088 or www.fda.gov/medwatch.

8 USE IN SPECIFIC POPULATIONS

• Pregnancy: Plasma levels of levetiracetam may be decreased and therefore need to be monitored closely during pregnancy. Based on animal data, may cause fetal harm (5.9, 8.1)
Revised: 03/13
Information describing the use of levetiracetam tablets and levetiracetam oral solution in pediatric patients less than 4 years of age as adjunctive therapy in the treatment of partial onset seizures is approved for UCB, Inc.’s levetiracetam tablets and oral solution. However, due to UCB Inc.’s marketing exclusivity rights, this drug product is not labeled with that pediatric information.

FULL PRESCRIBING INFORMATION

1 INDICATIONS AND USAGE

1.1 Partial Onset Seizures

Levetiracetam Oral Solution, USP is indicated as adjunctive therapy in the treatment of partial onset seizures in adults and children 4 years of age and older with epilepsy.

Information describing the use of levetiracetam in pediatric patients less than 4 years of age as adjunctive therapy in the treatment of partial onset seizures is approved for UCB, Inc.'s levetiracetam tablets and oral solution. However, due to UCB, Inc.'s marketing exclusivity rights, this drug product is not labeled with that pediatric information.

1.2 Myoclonic Seizures In Patients With Juvenile Myoclonic Epilepsy

Levetiracetam Oral Solution, USP is indicated as adjunctive therapy in the treatment of myoclonic seizures in adults and adolescents 12 years of age and older with juvenile myoclonic epilepsy.

1.3 Primary Generalized Tonic-Clonic Seizures

Levetiracetam Oral Solution, USP is indicated as adjunctive therapy in the treatment of primary generalized tonic-clonic seizures in adults and children 6 years of age and older with idiopathic generalized epilepsy.

2 DOSAGE AND ADMINISTRATION

2.1 Important Administration Instructions

Levetiracetam Oral Solution, USP is given orally with or without food. The levetiracetam dosing regimen depends on the indication, age group, dosage form, and renal function.

Prescribe the oral solution for pediatric patients with body weight ≤ 20 kg. Prescribe the oral solution or tablets for pediatric patients with body weight above 20 kg.

When using the oral solution in pediatric patients, dosing is weight-based (mg per kg) using a calibrated measuring device (not a household teaspoon or tablespoon).

2.2 Partial Onset Seizures

Adults 16 Years And Older

In clinical trials, daily doses of 1000 mg, 2000 mg, and 3000 mg, given as twice-daily dosing were shown to be effective. Although in some studies there was a tendency toward greater response with higher dose [see Clinical Studies (14.1)], a consistent increase in response with increased dose has not been shown.

Treatment should be initiated with a daily dose of 1000 mg/day, given as twice-daily dosing (500 mg twice daily). Additional dosing increments may be given (1000 mg/day additional every 2 weeks) to a maximum recommended daily dose of 3000 mg. Doses greater than 3000 mg/day have been used in open-label studies for periods of 6 months and longer. There is no evidence that doses greater than 3000 mg/day confer additional benefit.

Pediatric Patients

Dosing information in pediatric patients less than 4 years of age as adjunctive therapy in the treatment of partial onset seizures is approved for UCB, Inc.'s levetiracetam tablets and oral solution. However, due to UCB, Inc.'s marketing exclusivity rights, this drug product is not labeled with that pediatric information.

4 Years To < 16 Years

Treatment should be initiated with a daily dose of 20 mg/kg in 2 divided doses (10 mg/kg twice daily). The daily dose should be increased every 2 weeks by increments of 20 mg/kg to the recommended daily dose of 60 mg/kg (30 mg/kg twice daily). If a patient cannot tolerate a daily dose of 60 mg/kg, the daily dose may be reduced. In the clinical efficacy trial, the mean daily dose was 44 mg/kg. The maximum daily dose was 3000 mg/day.

Levetiracetam Oral Solution, USP Weight-Based Dosing Calculation For Pediatric Patients

The following calculation should be used to determine the appropriate daily dose of oral solution for pediatric patients:

Total daily dose (mL/day) = | Daily dose (mg/kg/day) × patient weight (kg)
Total daily dose (mL/day) = | 100 mg/mL

2.3 Myoclonic Seizures In Patients 12 Years Of Age And Older With Juvenile Myoclonic Epilepsy

Treatment should be initiated with a dose of 1000 mg/day, given as twice-daily dosing (500 mg twice daily). Dosage should be increased by 1000 mg/day every 2 weeks to the recommended daily dose of 3000 mg. The effectiveness of doses lower than 3000 mg/day has not been studied.

2.4 Primary Generalized Tonic-Clonic Seizures

Adults 16 Years And Older

Treatment should be initiated with a dose of 1000 mg/day, given as twice-daily dosing (500 mg twice daily). Dosage should be increased by 1000 mg/day every 2 weeks to the recommended daily dose of 3000 mg. The effectiveness of doses lower than 3000 mg/day has not been adequately studied.

Pediatric Patients Ages 6 To <16 Years

Treatment should be initiated with a daily dose of 20 mg/kg in 2 divided doses (10 mg/kg twice daily). The daily dose should be increased every 2 weeks by increments of 20 mg/kg to the recommended daily dose of 60 mg/kg (30 mg/kg twice daily). The effectiveness of doses lower than 60 mg/kg/day has not been adequately studied. Patients with body weight ≤ 20 kg should be dosed with oral solution. Patients with body weight above 20 kg can be dosed with either tablets or oral solution [see Dosage and Administration (2.1)].

2.5 Adult Patients With Impaired Renal Function

Levetiracetam dosing must be individualized according to the patient's renal function status. Recommended doses and adjustment for dose for adults are shown in Table 1. In order to calculate the dose recommended for patients with renal impairment, creatinine clearance adjusted for body surface area must be calculated. To do this an estimate of the patient's creatinine clearance (CLcr) in mL/min must first be calculated using the following formula:

CLcr = | [140-age (years)] × weight (kg) | (× 0.85 for female patients)
CLcr = | 72 × serum creatinine (mg/dL) | (× 0.85 for female patients)

Then CLcr is adjusted for body surface area (BSA) as follows:

CLcr (mL/min/1.73m^2 = | CLcr (mL/min) | × 1.73
CLcr (mL/min/1.73m^2 = | BSA subject (m2) | × 1.73

Table 1: Dosing Adjustment Regimen For Adult Patients With Impaired Renal Function
Group | Creatinine Clearance (mL/min/1.73m2) | Dosage (mg) | Frequency
Normal | > 80 | 500 to 1,500 | Every 12 hours
Mild | 50 – 80 | 500 to 1,000 | Every 12 hours
Moderate | 30 – 50 | 250 to 750 | Every 12 hours
Severe | < 30 | 250 to 500 | Every 12 hours
ESRD patients using dialysis | ---- | 500 to 1,000* | Every 24 hours*
* Following dialysis, a 250 to 500 mg supplemental dose is recommended.

3 DOSAGE FORMS AND STRENGTHS

Levetiracetam Oral Solution, USP, 100 mg/mL is a clear, colorless, grape-flavored liquid.

4 CONTRAINDICATIONS

Levetiracetam is contraindicated in patients with a hypersensitivity to levetiracetam. Reactions have included anaphylaxis and angioedema [see Warnings and Precautions (5.4)].

5 WARNINGS AND PRECAUTIONS

5.1 Psychiatric Reactions

In some patients levetiracetam causes behavioral abnormalities. The incidences of behavioral abnormalities in the myoclonic and primary generalized tonic-clonic seizure studies were comparable to those of the adult and pediatric partial onset seizure studies.

A total of 13.3% of adult levetiracetam-treated patients and 37.6% of pediatric levetiracetam-treated patients (4 to 16 years of age) compared to 6.2% and 18.6% of adult and pediatric placebo patients respectively, experienced non-psychotic behavioral symptoms (reported as aggression, agitation, anger, anxiety, apathy, depersonalization, depression, emotional lability, hostility, hyperkinesias, irritability, nervousness, neurosis, and personality disorder). A randomized double-blind, placebo-controlled study was performed to assess the neurocognitive and behavioral effects of levetiracetam as adjunctive therapy in pediatric patients (4 to 16 years of age). The results from an exploratory analysis indicated a worsening in levetiracetam-treated patients on aggressive behavior (one of eight behavior dimensions) as measured in a standardized and systematic way using a validated instrument, the Achenbach Child Behavior Checklist (CBCL/6-18).

In pediatric patients 1 month to < 4 years of age, irritability was reported in 11.7% of the levetiracetam-treated patients compared to 0% of placebo patients.

A total of 1.7% of adult levetiracetam-treated patients discontinued treatment due to behavioral adverse events, compared to 0.2% of placebo patients. The treatment dose was reduced in 0.8% of adult levetiracetam-treated patients and in 0.5% of placebo patients. Overall, 10.9% of levetiracetam-treated pediatric patients experienced behavioral symptoms associated with discontinuation or dose reduction, compared to 6.2% of placebo patients.

One percent of adult levetiracetam-treated patients, 2% of children 4 to 16 years of age, and 17% of children 1 month to <4 years of age experienced psychotic symptoms, compared to 0.2%, 2%, and 5% respectively, in the placebo patients. In the controlled study that assessed the neurocognitive and behavioral effects of levetiracetam in pediatric patients 4 to 16 years of age, 1 (1.6%) levetiracetam-treated patient experienced paranoia compared to no placebo patients. There were 2 (3.1%) levetiracetam-treated patients that experienced confusional state compared to no placebo patients [see Use in Specific Populations (8.4)].

Two (0.3%) adult levetiracetam-treated patients were hospitalized and their treatment was discontinued due to psychosis. Both events, reported as psychosis, developed within the first week of treatment and resolved within 1 to 2 weeks following treatment discontinuation. There was no difference between drug and placebo-treated patients in the incidence of the pediatric patients who discontinued treatment due to psychotic and non-psychotic adverse reactions.

The above psychiatric signs symptoms should be monitored.

5.2 Suicidal Behavior and Ideation

Antiepileptic drugs (AEDs), including levetiracetam, increase the risk of suicidal thoughts or behavior in patients taking these drugs for any indication. Patients treated with any AED for any indication should be monitored for the emergence or worsening of depression, suicidal thoughts or behavior, and/or any unusual changes in mood or behavior.

Pooled analyses of 199 placebo-controlled clinical trials (mono- and adjunctive therapy) of 11 different AEDs showed that patients randomized to one of the AEDs had approximately twice the risk (adjusted Relative Risk 1.8, 95% CI:1.2, 2.7) of suicidal thinking or behavior compared to patients randomized to placebo. In these trials, which had a median treatment duration of 12 weeks, the estimated incidence rate of suicidal behavior or ideation among 27,863 AED-treated patients was 0.43%, compared to 0.24% among 16,029 placebo-treated patients, representing an increase of approximately one case of suicidal thinking or behavior for every 530 patients treated. There were four suicides in drug-treated patients in the trials and none in placebo-treated patients, but the number is too small to allow any conclusion about drug effect on suicide.

The increased risk of suicidal thoughts or behavior with AEDs was observed as early as one week after starting drug treatment with AEDs and persisted for the duration of treatment assessed. Because most trials included in the analysis did not extend beyond 24 weeks, the risk of suicidal thoughts or behavior beyond 24 weeks could not be assessed.

The risk of suicidal thoughts or behavior was generally consistent among drugs in the data analyzed. The finding of increased risk with AEDs of varying mechanisms of action and across a range of indications suggests that the risk applies to all AEDs used for any indication. The risk did not vary substantially by age (5 to 100 years) in the clinical trials analyzed. Table 2 shows absolute and relative risk by indication for all evaluated AEDs.

Table 2: Risk by indication for antiepileptic drugs in the pooled analysis
Indication | Placebo Patients with Events Per 1000 Patients | Drug Patients with Events Per 1000 Patients | Relative Risk: Incidence of Events in Drug Patients / Incidence in Placebo Patients | Risk Difference: Additional Drug Patients with Events Per 1000 Patients
Epilepsy | 1.0 | 3.4 | 3.5 | 2.4
Psychiatric | 5.7 | 8.5 | 1.5 | 2.9
Other | 1.0 | 1.8 | 1.9 | 0.9
Total | 2.4 | 4.3 | 1.8 | 1.9

The relative risk for suicidal thoughts or behavior was higher in clinical trials for epilepsy than in clinical trials for psychiatric or other conditions, but the absolute risk differences were similar for the epilepsy and psychiatric indications.

Anyone considering prescribing levetiracetam or any other AED must balance the risk of suicidal thoughts or behaviors with the risk of untreated illness. Epilepsy and many other illnesses for which AEDs are prescribed are themselves associated with morbidity and mortality and an increased risk of suicidal thoughts and behavior. Should suicidal thoughts and behavior emerge during treatment, the prescriber needs to consider whether the emergence of these symptoms in any given patient may be related to the illness being treated. Patients, their caregivers, and families should be informed that AEDs increase the risk of suicidal thoughts and behavior and should be advised of the need to be alert for the emergence or worsening of the signs and symptoms of depression, any unusual changes in mood or behavior, or the emergence of suicidal thoughts, behavior, or thoughts about self-harm. Behaviors of concern should be reported immediately to healthcare providers.

5.3 Somnolence and Fatigue

In some patients, levetiracetam causes somnolence and fatigue. The incidences of somnolence and fatigue provided below are from controlled adult partial onset seizure studies. In general, the incidences of somnolence and fatigue in the pediatric partial onset seizure studies, and in pediatric and adult myoclonic and primary generalized tonic-clonic seizure studies were comparable to those of the adult partial onset seizure studies.

In controlled trials of adult patients with epilepsy experiencing partial onset seizures, 14.8% of levetiracetam-treated patients reported somnolence, compared to 8.4% of placebo patients. There was no clear dose response up to 3000 mg/day. In a study where there was no titration, about 45% of patients receiving 4000 mg/day reported somnolence. The somnolence was considered serious in 0.3% of the treated patients, compared to 0% in the placebo group. About 3% of levetiracetam-treated patients discontinued treatment due to somnolence, compared to 0.7% of placebo patients. In 1.4% of treated patients and in 0.9% of placebo patients the dose was reduced, while 0.3% of the treated patients were hospitalized due to somnolence.

In controlled trials of adult patients with epilepsy experiencing partial onset seizures, 14.7% of levetiracetam-treated patients reported asthenia, compared to 9.1% of placebo patients. Treatment was discontinued due to asthenia in 0.8% of treated patients as compared to 0.5% of placebo patients. In 0.5% of treated patients and in 0.2% of placebo patients the dose was reduced due to asthenia.

Somnolence and asthenia occurred most frequently within the first 4 weeks of treatment.

Patients should be monitored for these signs and symptoms and advised not to drive or operate machinery until they have gained sufficient experience on levetiracetam to gauge whether it adversely affects their ability to drive or operate machinery.

5.4 Anaphylaxis and Angioedema

Le veti racet am can cause anaphylaxis or angioedema after the first dose or at any time during treatment. Signs and symptoms in cases reported in the postmarketing setting have included hypotension, hives, rash, respiratory distress, and swelling of the face, lip, mouth, eye, tongue, throat, and feet. In some reported cases, reactions were lifethreatening and required emergency treatment. If a patient develops signs or symptoms of anaphylaxis or angioedema, le veti racetam should be discontinued and the patient should seek immediate medical attention. le veti racetam should be discontinued permanently if a clear alternative etiology for the reaction cannot be established [see Contraindications (4)].

5.5 Serious Dermatological Reactions

Serious dermatological reactions, including Stevens-Johnson syndrome (SJS) and toxic epidermal necrolysis (TEN), have been reported in both children and adults treated with levetiracetam. The median time of onset is reported to be 14 to 17 days, but cases have been reported at least four months after initiation of treatment. Recurrence of the serious skin reactions following rechallenge with levetiracetam has also been reported. Levetiracetam should be discontinued at the first sign of a rash, unless the rash is clearly not drug-related. If signs or symptoms suggest SJS/TEN, use of this drug should not be resumed and alternative therapy should be considered.

5.6 Coordination Difficulties

Coordination difficulties were only observed in the adult partial onset seizure studies. A total of 3.4% of adult levetiracetam-treated patients experienced coordination difficulties, (reported as either ataxia, abnormal gait, or incoordination) compared to 1.6% of placebo patients. A total of 0.4% of patients in controlled trials discontinued levetiracetam treatment due to ataxia, compared to 0% of placebo patients. In 0.7% of treated patients and in 0.2% of placebo patients the dose was reduced due to coordination difficulties, while one of the treated patients was hospitalized due to worsening of pre-existing ataxia. These events occurred most frequently within the first 4 weeks of treatment.

Patients should be monitored for these signs and symptoms and advised not to drive or operate machinery until they have gained sufficient experience on levetiracetam to gauge whether it could adversely affect their ability to drive or operate machinery.

5.7 Withdrawal Seizures

Antiepileptic drugs, including levetiracetam, should be withdrawn gradually to minimize the potential of increased seizure frequency.

5.8 Hematologic Abnormalities

Levetriacetam can cause hematologic abnormalities. Hematologic abnormalities occurred in clinical trials and included decreases in white blood cell (WBC), neutrophil, and red blood cell (RBC) counts; decreases in hemoglobin and hematocrit; and increases in eosinophil counts. Cases of agranulocytosis, pancytopenia, and thrombocytopenia have been reported in the postmarketing setting. A complete blood count is recommended in patients experiencing significant weakness, pyrexia, recurrent infections, or coagulation disorders.

Partial Onset Seizures

Adults
Minor, but statistically significant, decreases compared to placebo in total mean RBC count (0.03 × 10^6/mm^3), mean hemoglobin (0.09 g/dL), and mean hematocrit (0.38%), were seen in levetiracetam-treated patients in controlled trials.

A total of 3.2% of treated and 1.8% of placebo patients had at least one possibly significant (≤ 2.8 × 10^9/L) decreased WBC, and 2.4% of treated and 1.4% of placebo patients had at least one possibly significant (≤ 1.0 × 10^9/L) decreased neutrophil count. Of the treated patients with a low neutrophil count, all but one rose towards or to baseline with continued treatment. No patient was discontinued secondary to low neutrophil counts.

Pediatric Patients 4 Years To < 16 Years

Statistically significant decreases in WBC and neutrophil counts were seen in levetiracetam-treated patients as compared to placebo. The mean decreases from baseline in the levetiracetam-treated group were -0.4 × 10^9/L and 0.3 × 10^9/L, respectively, whereas there were small increases in the placebo group. Mean relative lymphocyte counts increased by 1.7% in levetiracetam-treated patients, compared to a decrease of 4% in placebo patients (statistically significant).

In the controlled trial, more levetiracetam-treated patients had a possibly clinically significant abnormally low WBC value (3.0% levetiracetam-treated versus 0% placebo), however, there was no apparent difference between treatment groups with respect to neutrophil count (5.0% levetiracetam-treated versus 4.2% placebo). No patient was discontinued secondary to low WBC or neutrophil counts.

In the controlled cognitive and neuropsychological safety study, two subjects (6.1%) in the placebo group and 5 subjects (8.6%) in the levetiracetam-treated group had high eosinophil count values that were possibly clinically significant (≥10% or ≥0.7×10^9/L).

Juvenile Myoclonic Epilepsy

Although there were no obvious hematologic abnormalities observed in patients with JME, the limited number of patients makes any conclusion tentative. The data from the partial seizure patients should be considered to be relevant for JME patients.

5.9 Blood Pressure Increases

In a randomized, placebo-controlled study in patients aged 1 month to <4 years of age, a significantly higher risk of at least one measured increase in diastolic blood pressure was observed in the levetiracetam-treated patients (17%) compared to the placebo treated patients (2%). There was no overall difference in mean diastolic blood pressure between the treatment groups. This disparity between the levetiracetam and placebo treatment groups was not observed in the studies of older children or in adults.

5.10 Seizure Control During Pregnancy

Physiological changes may gradually decrease plasma levels of levetiracetam throughout pregnancy. This decrease is more pronounced during the third trimester. It is recommended that patients be monitored carefully during pregnancy. Close monitoring should continue through the postpartum period especially if the dose was changed during pregnancy.

6 ADVERSE REACTIONS

The following adverse reactions are discussed in more details in other sections of labeling:

- Psychiatric Symptoms[see Warnings and Precautions (5.1)]
- Suicidal Behavior and Ideation [see Warnings and Precautions (5.2)]
- Somnolence and Fatigue [see Warnings and Precautions (5.3)]
- Serious Dermatological Reactions [see Warnings and Precautions (5.4)]
- Coordination Difficulties [see Warnings and Precautions (5.5)]
- Withdrawal Seizures [see Warnings and Precautions (5.6)]
- Hematologic Abnormalities[see Warnings and Precautions (5.7)]
- Blood Pressure Increases [see Warnings and Precautions (5.8)]
- Seizure Control During Pregnancy[see Warnings and Precautions (5.9)]

6.1 Clinical Trials Experience

Because clinical trials are conducted under widely varying conditions, adverse reaction rates observed in the clinical trials of a drug cannot be directly compared to rates in the clinical trials of another drug and may not reflect the rates observed in practice.

The prescriber should be aware that the adverse reaction incidence figures in the following tables, obtained when levetiracetam was added to concurrent AED therapy, cannot be used to predict the frequency of adverse reactions in the course of usual medical practice where patient characteristics and other factors may differ from those prevailing during clinical trials. Similarly, the cited frequencies cannot be directly compared with figures obtained from other clinical investigations involving different treatments, uses, or investigators. An inspection of these frequencies, however, does provide the prescriber with one basis to estimate the relative contribution of drug and non-drug factors to the adverse reaction incidences in the population studied.

Partial Onset Seizures

Adults

In controlled clinical studies in adults with partial onset seizures, the most frequently reported adverse reactions in patients receiving levetiracetam in combination with other AEDs were somnolence, asthenia, infection and dizziness. Of the most frequently reported adverse reactions in adults experiencing partial onset seizures, asthenia, somnolence and dizziness appeared to occur predominantly during the first 4 weeks of treatment with levetiracetam.

Table 3 lists adverse reactions that occurred in at least 1% of adult epilepsy patients treated with levetiracetam participating in placebo-controlled studies and were numerically more common than in patients treated with placebo. In these studies, either levetiracetam or placebo was added to concurrent AED therapy. Adverse reactions were usually mild to moderate in intensity.

Table 3: Incidence (%) Of Adverse Reactions In Placebo-Controlled, Add-On Studies In Adults Experiencing Partial Onset Seizures By Body System (Adverse Reactions Occurred In At Least 1% Of Levetiracetam-Treated Patients And Occurred More Frequently Than Placebo-Treated Patients)
Body System/ Adverse Reaction | Levetiracetam (N=769) % | Placebo (N=439) %
Body as a Whole
Asthenia | 15 | 9
Headache | 14 | 13
Infection | 13 | 8
Pain | 7 | 6
Digestive System
Anorexia | 3 | 2
Nervous System
Somnolence | 15 | 8
Dizziness | 9 | 4
Depression | 4 | 2
Nervousness | 4 | 2
Ataxia | 3 | 1
Vertigo | 3 | 1
Amnesia | 2 | 1
Anxiety | 2 | 1
Hostility | 2 | 1
Paresthesia | 2 | 1
Emotional Lability | 2 | 0
Respiratory System
Pharyngitis | 6 | 4
Rhinitis | 4 | 3
Cough Increased | 2 | 1
Sinusitis | 2 | 1
Special Senses
Diplopia | 2 | 1

In controlled adult clinical studies, 15% of patients receiving levetiracetam and 12% receiving placebo either discontinued or had a dose reduction as a result of an adverse event. Table 4 lists the most common (>1%) adverse reactions that resulted in discontinuation or dose reduction and that occurred more frequently in levetiracetam-treated patients than in placebo-treated patients.

Table 4: Adverse Reactions That Most Commonly Resulted In Discontinuation Or Dose Reduction That Occurred More Frequently In Levetiracetam-Treated Patients In Placebo-Controlled Studies In Adult Patients Experiencing Partial Onset Seizures
Adverse Reaction | Levetiracetam (N=769) % | Placebo (N=439) %
Dizziness | 1 | 0
Somnolence | 4 | 2

Pediatric Patients 4 Years To <16 Years

The adverse reaction data presented below was obtained from a pooled analysis of two controlled pediatric clinical studies in children 4 to 16 years of age with partial onset seizures. The adverse reactions most frequently reported with the use of levetiracetam in combination with other AEDs, not seen at an equivalent frequency among placebo-treated patients, were fatigue, aggression, nasal congestion, decreased appetite, and irritability.

Table 5 lists adverse reactions from the pooled pediatric controlled studies (4 to 16 years of age) that occurred in at least 2% of pediatric levetiracetam-treated patients and were numerically more common than in pediatric patients treated with placebo. In these studies, either levetiracetam or placebo was added to concurrent AED therapy. Adverse reactions were usually mild to moderate in intensity.

Table 5: Incidence (%) Of Adverse Reactions In Pooled Placebo-Controlled, Add-On Studies In Pediatric Patients Ages 4 to 16 Years Experiencing Partial Onset Seizures By Body System (Adverse Reactions Occurred In At Least 2% Of Levetiracetam-Treated Patients And Occurred More Frequently Than Placebo-Treated Patients)
Body System/ Adverse Reaction | Levetiracetam (N=165) % | Placebo (N=131) %
Ear and Labyrinth Disorders
Ear Pain | 2 | 1
Eye Disorders
Conjunctivitis | 2 | 0
Gastrointestinal Disorders
Vomiting | 15 | 12
Abdominal Pain Upper | 9 | 8
Diarrhea | 6 | 5
Constipation | 3 | 1
General Disorders and Administration Site Conditions
Fatigue | 11 | 5
Infections and Infestations
Nasopharyngitis | 15 | 12
Influenza | 3 | 1
Gastroenteritis | 2 | 0
Rhinitis | 2 | 0
Injury, Poisoning and Procedural Complications
Head Injury | 4 | 0
Contusion | 3 | 1
Fall | 3 | 2
Joint Sprain | 2 | 1
Metabolism and Nutrition Disorders
Decreased Appetite | 8 | 2
Anorexia | 4 | 3
Musculoskeletal and Connective Tissue Disorders
Arthralgia | 2 | 0
Neck Pain | 2 | 1
Nervous System
Headache | 19 | 15
Somnolence | 13 | 9
Dizziness | 7 | 5
Lethargy | 6 | 2
Sedation | 2 | 1
Psychiatric Disorders
Aggression | 10 | 5
Abnormal Behavior | 7 | 4
Irritability | 7 | 1
Insomnia | 5 | 3
Agitation | 4 | 1
Depression | 3 | 1
Mood Altered | 3 | 1
Affect Lability | 2 | 1
Anxiety | 2 | 1
Confusional State | 2 | 0
Mood Swings | 2 | 1
Respiratory, Thoracic and Mediastinal Disorders
Cough | 9 | 5
Nasal Congestion | 9 | 2
Pharyngolaryngeal Pain | 7 | 4

In the well-controlled pooled pediatric clinical studies in patients 4 to 16 years of age, 7% of patients receiving levetiracetam and 9% receiving placebo discontinued as a result of an adverse event.

Adverse reaction information in pediatric patients less than 4 years of age as adjunctive therapy in the treatment of partial onset seizures is approved for UCB, Inc.'s levetiracetam tablets and oral solution. However, due to UCB, Inc.'s marketing exclusivity rights, this drug product is not labeled with that pediatric information.

Myoclonic Seizures

Although the pattern of adverse reactions in this study seems somewhat different from that seen in patients with partial seizures, this is likely due to the much smaller number of patients in this study compared to partial seizure studies. The adverse reaction pattern for patients with JME is expected to be essentially the same as for patients with partial seizures.

In the well-controlled clinical study that included both adolescent (12 to 16 years of age) and adult patients with myoclonic seizures, the most frequently reported adverse reactions in patients using levetiracetam in combination with other AEDs, not seen at an equivalent frequency among placebo-treated patients, were somnolence, neck pain, and pharyngitis.

Table 7 lists adverse reactions that occurred in at least 5% of juvenile myoclonic epilepsy patients experiencing myoclonic seizures treated with levetiracetam and were numerically more common than in patients treated with placebo. In this study, either levetiracetam or placebo was added to concurrent AED therapy. Adverse reactions were usually mild to moderate in intensity.

Table 7: Incidence (%) Of Adverse Reactions In A Placebo-Controlled, Add-On Study In Patients 12 Years Of Age And Older With Myoclonic Seizures By Body System (Adverse Reactions Occurred In At Least 5% Of Levetiracetam-Treated Patients And Occurred More Frequently Than Placebo-Treated Patients)
Body System/ Adverse Reaction | Levetiracetam (N=60) % | Placebo (N=60) %
Ear and labyrinth disorders
Vertigo | 5 | 3
Infections and infestations
Pharyngitis | 7 | 0
Influenza | 5 | 2
Musculoskeletal and connective tissue disorders
Neck pain | 8 | 2
Nervous system disorders
Somnolence | 12 | 2
Psychiatric disorders
Depression | 5 | 2

In the placebo-controlled study, 8% of patients receiving levetiracetam and 2% receiving placebo either discontinued or had a dose reduction as a result of an adverse reaction. The adverse reactions that led to discontinuation or dose reduction in the well-controlled study and occurred more frequently in levetiracetam-treated patients than in placebo-treated patients are presented in Table 8.

Table 8: Adverse Reactions That Resulted In Discontinuation Or Dose Reduction That Occurred More Frequently in Levetiracetam-Treated Patients In The Placebo-Controlled Study In Patients With Juvenile Myoclonic Epilepsy
Adverse Reaction | Levetiracetam (N=60) % | Placebo (N=60) %
Anxiety | 3 | 2
Depressed Mood | 2 | 0
Depression | 2 | 0
Diplopia | 2 | 0
Hypersomnia | 2 | 0
Insomnia | 2 | 0
Irritability | 2 | 0
Nervousness | 2 | 0
Somnolence | 2 | 0

Primary Generalized Tonic-Clonic Seizures

Although the pattern of adverse reactions in this study seems somewhat different from that seen in patients with partial seizures, this is likely due to the much smaller number of patients in this study compared to partial seizure studies. The adverse reaction pattern for patients with PGTC seizures is expected to be essentially the same as for patients with partial seizures.

In the well-controlled clinical study that included patients 4 years of age and older with primary generalized tonic-clonic (PGTC) seizures, the most frequently reported adverse reaction in patients using levetiracetam in combination with other AEDs, not seen at an equivalent frequency among placebo-treated patients, was nasopharyngitis.

Table 9 lists adverse reactions that occurred in at least 5% of idiopathic generalized epilepsy patients experiencing PGTC seizures treated with levetiracetam and were numerically more common than in patients treated with placebo. In this study, either levetiracetam or placebo was added to concurrent AED therapy. Adverse reactions were usually mild to moderate in intensity.

Table 9: Incidence (%) Of Adverse Reactions In A Placebo-Controlled, Add-On Study In Patients 4 Years Of Age And Older With PGTC Seizures By MedDRA System Organ Class (Adverse Reactions Occurred In At Least 5% Of Levetiracetam-Treated Patients And Occurred More Frequently Than Placebo-Treated Patients)
Body System/ Adverse Reaction | Levetiracetam (N=79) % | Placebo (N=84) %
Gastrointestinal disorders
Diarrhea | 8 | 7
General disorders and administration site conditions
Fatigue | 10 | 8
Infections and infestations
Nasopharyngitis | 14 | 5
Psychiatric disorders
Irritability | 6 | 2
Mood Swings | 5 | 1

In the placebo-controlled study, 5% of patients receiving levetiracetam and 8% receiving placebo either discontinued or had a dose reduction during the treatment period as a result of an adverse reaction.

This study was too small to adequately characterize the adverse reactions that could be expected to result in discontinuation of treatment in this population. It is expected that the adverse reactions that would lead to discontinuation in this population would be similar to those resulting in discontinuation in other epilepsy trials (see tables 4 and 8).

In addition, the following adverse reactions were seen in other well-controlled adult studies of levetiracetam: balance disorder, disturbance in attention, eczema, memory impairment, myalgia, and vision blurred.

Comparison Of Gender, Age And Race

The overall adverse reaction profile of levetiracetam was similar between females and males. There are insufficient data to support a statement regarding the distribution of adverse experience reports by age and race.

6.2 Postmarketing Experience

The following adverse reactions have been identified during postapproval use of levetiracetam. Because these reactions are reported voluntarily from a population of uncertain size, it is not always possible to reliably estimate their frequency or establish a causal relationship to drug exposure.

In addition to the adverse reactions listed above, [see Adverse Reactions (6.1)], the following adverse events have been reported in patients receiving marketed levetiracetam worldwide. The listing is alphabetized: abnormal liver function test, acute kidney injury, anaphylaxis, angioedema, agranulocytosis, choreoathetosis, drug reaction with eosinophilia and systemic symptoms (DRESS), dyskinesia, erythema multiforme, hepatic failure, hepatitis, leukopenia, neutropenia, pancreatitis, pancytopenia (with bone marrow suppression identified in some of these cases), panic attack, thrombocytopenia, and weight loss. Alopecia has been reported with levetiracetam use; recovery was observed in majority of cases where levetiracetam was discontinued.

7 DRUG INTERACTIONS

No significant pharmacokinetic interactions were observed between levetiracetam or its major metabolite and concomitant medications via human liver cytochrome P450 isoforms, epoxide hydrolase, UDP-glucuronidation enzymes, P-glycoprotein, or renal tubular secretion [see Clinical Pharmacology (12.3)].

8 USE IN SPECIFIC POPULATIONS

8.1 Pregnancy

Levetiracetam levels may decrease during pregnancy [see Warnings and Precautions (5.9)].

Pregnancy Category C

There are no adequate and well-controlled studies in pregnant women. In animal studies, levetiracetam produced evidence of developmental toxicity, including teratogenic effects, at doses similar to or greater than human therapeutic doses. Levetiracetam should be used during pregnancy only if the potential benefit justifies the potential risk to the fetus.

Oral administration of levetiracetam to female rats throughout pregnancy and lactation led to increased incidences of minor fetal skeletal abnormalities and retarded offspring growth pre- and/or postnatally at doses ≥350 mg/kg/day (equivalent to the maximum recommended human dose of 3000 mg [MRHD] on a mg/m^2 basis) and with increased pup mortality and offspring behavioral alterations at a dose of 1800 mg/kg/day (6 times the MRHD on a mg/m2 basis). The developmental no effect dose was 70 mg/kg/day (0.2 times the MRHD on a mg/m^2basis). There was no overt maternal toxicity at the doses used in this study.

Oral administration of levetiracetam to pregnant rabbits during the period of organogenesis resulted in increased embryofetal mortality and increased incidences of minor fetal skeletal abnormalities at doses ≥600 mg/kg/day (4 times MRHD on a mg/m^2 basis) and in decreased fetal weights and increased incidences of fetal malformations at a dose of 1800 mg/kg/day (12 times the MRHD on a mg/m^2 basis). The developmental no effect dose was 200 mg/kg/day (equivalent to the MRHD on a mg/m^2 basis). Maternal toxicity was also observed at 1800 mg/kg/day.

When levetiracetam was administered orally to pregnant rats during the period of organogenesis, fetal weights were decreased and the incidence of fetal skeletal variations was increased at a dose of 3600 mg/kg/day (12 times the MRHD). 1200 mg/kg/day (4 times the MRHD) was a developmental no effect dose. There was no evidence of maternal toxicity in this study.

Treatment of rats with levetiracetam during the last third of gestation and throughout lactation produced no adverse developmental or maternal effects at doses of up to 1800 mg/kg/day (6 times the MRHD on a mg/m^2 basis).

Pregnancy Registry

To provide information regarding the effects of in utero exposure to levetiracetam, physicians are advised to recommend that pregnant patients taking levetiracetam enroll in the North American Antiepileptic Drug (NAAED) pregnancy registry. This can be done by calling the toll free number 1-888-233-2334, and must be done by the patients themselves. Information on the registry can also be found at the website http://www.aedpregnancyregistry.org/.

8.2 Labor And Delivery

The e ffect of le veti racetam on la bor a nd deli v e ry in hum a ns is u nknow n.

8.3 Nursing Mothers

Levetiracetam is excreted in human milk. Because of the potential for serious adverse reactions in nursing infants from levetiracetam, a decision should be made whether to discontinue nursing or dscontinue the drug, taking into account the importance of the drug to the mother.

8.4 Pediatric Use

The safety and effectiveness of levetiracetam in the adjunctive treatment of partial onset seizures in pediatric patients age 4 years to 16 years old with epilepsy have been established [see Clinical Studies (14.1)]. The dosing recommendation in these pediatric patients varies according to age group and is weight-based [see Dosage and Administration (2.2)].

Pediatric use information in pediatric patients less than 4 years of age as adjunctive therapy in the treatment of partial onset seizures is approved for UCB, Inc.'s levetiracetam tablets and oral solution. However, due to UCB, Inc.'s marketing exclusivity rights, this drug product is not labeled with that pediatric information.

The safety and effectiveness of levetiracetam as adjunctive treatment of myoclonic seizures in adolescents 12 years of age and older with juvenile myoclonic epilepsy have been established [see Clinical Studies (14.2)].

The safety and effectiveness of levetiracetam as adjunctive therapy in the treatment of primary generalized tonic-clonic seizures in pediatric patients 6 years of age and older with idiopathic generalized epilepsy have been established [see Clinical Studies (14.3)].

A 3-month, randomized, double-blind, placebo-controlled study was performed to assess the neurocognitive and behavioral effects of levetiracetam as adjunctive therapy in 98 (levetiracetam N=64, placebo N=34) pediatric patients, ages 4 to 16 years old, with partial seizures that were inadequately controlled. The target dose was 60 mg/kg/day. Neurocognitive effects were measured by the Leiter-R Attention and Memory (AM) Battery, which measures various aspects of a child's memory and attention. Although no substantive differences were observed between the placebo and drug treated groups in the median change from baseline in this battery, the study was not adequate to assess formal statistical non-inferiority of the drug and placebo. The Achenbach Child Behavior Checklist (CBCL/6-18), a standardized validated tool used to assess a child's competencies and behavioral/emotional problems, was also assessed in this study. An analysis of the CBCL/6-18 indicated on average a worsening in levetiracetam-treated patients in aggressive behavior, one of the eight syndrome scores. [see Warnings and Precautions (5.1)]

Studies of levetiracetam in juvenile rats (dosing from day 4 through day 52 of age) and dogs (dosing from week 3 through week 7 of age) at doses of up to 1800 mg/kg/day (approximately 7 and 24 times, respectively, the maximum recommended pediatric dose of 60 mg/kg/day on a mg/m^2basis) did not indicate a potential for age-specific toxicity.

8.5 Geriatric Use

There were 347 subjects in clinical studies of levetiracetam that were 65 and over. No overall differences in safety were observed between these subjects and younger subjects. There were insufficient numbers of elderly subjects in controlled trials of epilepsy to adequately assess the effectiveness of levetiracetam in these patients. Levetiracetam is known to be substantially excreted by the kidney, and the risk of adverse reactions to this drug may be greater in patients with impaired renal function. Because elderly patients are more likely to have decreased renal function, care should be taken in dose selection, and it may be useful to monitor renal function[see Clinical Pharmacology (12.3)].

8.6 Use In Patients With Impaired Renal Function

Clearance of levetiracetam is decreased in patients with renal impairment and is correlated with creatinine clearance [see Clinical Pharmacology (12.3)]. Dose adjustment is recommended for patients with impaired renal function and supplemental doses should be given to patients after dialysis [see Dosage and Administration (2.5)].

10 OVERDOSAGE

10.1 Signs, Symptoms And Laboratory Findings Of Acute

The highest known dose of levetiracetam received in the clinical development program was 6000 mg/day. Other than drowsiness, there were no adverse events in the few known cases of overdose in clinical trials. Cases of somnolence, agitation, aggression, depressed level of consciousness, respiratory depression and coma were observed with levetiracetam overdoses in postmarketing use.

10.2 Management Of Overdose

There is no specific antidote for overdose with levetiracetam. If indicated, elimination of unabsorbed drug should be attempted by emesis or gastric lavage; usual precautions should be observed to maintain airway. General supportive care of the patient is indicated including monitoring of vital signs and observation of the patient's clinical status. A Certified Poison Control Center should be contacted for up to date information on the management of overdose with levetiracetam.

10.3 Hemodialysis

Standard hemodialysis procedures result in significant clearance of levetiracetam (approximately 50% in 4 hours) and should be considered in cases of overdose. Although hemodialysis has not been performed in the few known cases of overdose, it may be indicated by the patient's clinical state or in patients with significant renal impairment.

11 DESCRIPTION

Levetiracetam Oral Solution, USP is an antiepileptic drug available as a clear, colorless, grape-flavored liquid (100 mg/mL) for oral administration. The chemical name of levetiracetam, a single enantiomer, is (-)-(S)-α-ethyl-2-oxo-1-pyrrolidine acetamide, its molecular formula is C8H14N2O2 and its molecular weight is 170.21. Levetiracetam is chemically unrelated to existing antiepileptic drugs (AEDs). It has the following structural formula:

Levetiracetam is a white to off-white crystalline powder with a faint odor and a bitter taste. It is very soluble in water (104.0 g/100 mL). It is freely soluble in chloroform (65.3 g/100 mL) and in methanol (53.6 g/100 mL), soluble in ethanol (16.5 g/100 mL), sparingly soluble in acetonitrile (5.7 g/100 mL) and practically insoluble in n-hexane. (Solubility limits are expressed as g/100 mL solvent.) Levetiracetam Oral Solution, USP contains 100 mg of levetiracetam per mL. Inactive ingredients: acesulfame potassium, artificial grape flavor, citric acid, glycerin, maltitol solution, methylparaben, monoammonium glycyrrhizinate, propylparaben, purified water, sodium citrate.

12 CLINICAL PHARMACOLOGY

12.1 Mechanism of Action

The precise mechanism(s) by which levetiracetam exerts its antiepileptic effect is unknown. The antiepileptic activity of levetiracetam was assessed in a number of animal models of epileptic seizures. Levetiracetam did not inhibit single seizures induced by maximal stimulation with electrical current or different chemoconvulsants and showed only minimal activity in submaximal stimulation and in threshold tests. Protection was observed, however, against secondarily generalized activity from focal seizures induced by pilocarpine and kainic acid, two chemoconvulsants that induce seizures that mimic some features of human complex partial seizures with secondary generalization. Levetiracetam also displayed inhibitory properties in the kindling model in rats, another model of human complex partial seizures, both during kindling development and in the fully kindled state. The predictive value of these animal models for specific types of human epilepsy is uncertain.

In vitro and in vivo recordings of epileptiform activity from the hippocampus have shown that levetiracetam inhibits burst firing without affecting normal neuronal excitability, suggesting that levetiracetam may selectively prevent hypersynchronization of epileptiform burst firing and propagation of seizure activity.

Levetiracetam at concentrations of up to 10 μM did not demonstrate binding affinity for a variety of known receptors, such as those associated with benzodiazepines, GABA (gamma-aminobutyric acid), glycine, NMDA (N-methyl-D-aspartate), re-uptake sites, and second messenger systems. Furthermore, in vitrostudies have failed to find an effect of levetiracetam on neuronal voltage-gated sodium or T-type calcium currents and levetiracetam does not appear to directly facilitate GABAergic neurotransmission. However, in vitrostudies have demonstrated that levetiracetam opposes the activity of negative modulators of GABA- and glycine-gated currents and partially inhibits N-type calcium currents in neuronal cells.

A saturable and stereoselective neuronal binding site in rat brain tissue has been described for levetiracetam. Experimental data indicate that this binding site is the synaptic vesicle protein SV2A, thought to be involved in the regulation of vesicle exocytosis. Although the molecular significance of levetiracetam binding to SV2A is not understood, levetiracetam and related analogs showed a rank order of affinity for SV2A which correlated with the potency of their antiseizure activity in audiogenic seizure-prone mice. These findings suggest that the interaction of levetiracetam with the SV2A protein may contribute to the antiepileptic mechanism of action of the drug.

12.2 Pharmacodynamics

Effects on QTc Interval

The effect of levetiracetam on QTc prolongation was evaluated in a randomized, double-blind, positive-controlled (moxifloxacin 400 mg) and placebo-controlled crossover study of levetiracetam (1000 mg or 5000 mg) in 52 healthy subjects. The upper bound of the 90% confidence interval for the largest placebo-adjusted, baseline-corrected QTc was below 10 milliseconds. Therefore, there was no evidence of significant QTc prolongation in this study.

12.3 Pharmacokinetics

Absorption and Distribution

Absorption of levetiracetam is rapid, with peak plasma concentrations occurring in about an hour following oral administration in fasted subjects. The oral bioavailability of levetiracetam tablets is 100% and the tablets and oral solution are bioequivalent in rate and extent of absorption. Food does not affect the extent of absorption of levetiracetam but it decreases Cmax by 20% and delays Tmax by 1.5 hours. The pharmacokinetics of levetiracetam are linear over the dose range of 500 to 5000 mg. Steady state is achieved after 2 days of multiple twice-daily dosing. Levetiracetam and its major metabolite are less than 10% bound to plasma proteins; clinically significant interactions with other drugs through competition for protein binding sites are therefore unlikely.

Metabolism

Levetiracetam is not extensively metabolized in humans. The major metabolic pathway is the enzymatic hydrolysis of the acetamide group, which produces the carboxylic acid metabolite, ucb L057 (24% of dose) and is not dependent on any liver cytochrome P450 isoenzymes. The major metabolite is inactive in animal seizure models. Two minor metabolites were identified as the product of hydroxylation of the 2-oxo-pyrrolidine ring (2% of dose) and opening of the 2-oxo-pyrrolidine ring in position 5 (1% of dose). There is no enantiomeric interconversion of levetiracetam or its major metabolite.

Elimination

Levetiracetam plasma half-life in adults is 7 ± 1 hour and is unaffected by either dose or repeated administration. Levetiracetam is eliminated from the systemic circulation by renal excretion as unchanged drug which represents 66% of administered dose. The total body clearance is 0.96 mL/min/kg and the renal clearance is 0.6 mL/min/kg. The mechanism of excretion is glomerular filtration with subsequent partial tubular reabsorption. The metabolite ucb L057 is excreted by glomerular filtration and active tubular secretion with a renal clearance of 4 mL/min/kg. Levetiracetam elimination is correlated to creatinine clearance. Levetiracetam clearance is reduced in patients with impaired renal function [see Use in Specific Populations (8.6) and Dosage and Administration (2.5)].

Specific Populations:

Elderly

Pharmacokinetics of levetiracetam were evaluated in 16 elderly subjects (age 61 to 88 years) with creatinine clearance ranging from 30 to 74 mL/min. Following oral administration of twice-daily dosing for 10 days, total body clearance decreased by 38% and the half-life was 2.5 hours longer in the elderly compared to healthy adults. This is most likely due to the decrease in renal function in these subjects.

Pediatric Patients

Pharmacokinetics of levetiracetam were evaluated in 24 pediatric patients (age 6 to 12 years) after single dose (20 mg/kg). The body weight adjusted apparent clearance of levetiracetam was approximately 40% higher than in adults.

A repeat dose pharmacokinetic study was conducted in pediatric patients (age 4 to 12 years) at doses of 20 mg/kg/day, 40 mg/kg/day, and 60 mg/kg/day. The evaluation of the pharmacokinetic profile of levetiracetam and its metabolite (ucb L057) in 14 pediatric patients demonstrated rapid absorption of levetiracetam at all doses with a Tmax of about 1 hour and a t1/2 of 5 hours across the three dosing levels. The pharmacokinetics of levetiracetam in children was linear between 20 to 60 mg/kg/day. The potential interaction of levetiracetam with other AEDs was also evaluated in these patients. Levetiracetam had no significant effect on the plasma concentrations of carbamazepine, valproic acid, topiramate or lamotrigine. However, there was about a 22% increase of apparent clearance of levetiracetam when it was co-administered with an enzyme-inducing AED (e.g. carbamazepine).

Pharmacokinetics information in pediatric patients less than 4 years of age is approved for UCB, Inc.'s levetiracetam tablets and oral solution. However, due to UCB, Inc.'s marketing exclusivity rights, this drug product is not labeled with that pediatric information.

Population pharmacokinetic analysis showed that body weight was significantly correlated to the clearance of levetiracetam in pediatric patients; clearance increased with an increase in body weight.

Pregnancy

Levetiracetam levels may decrease during pregnancy.

Gender

Levetiracetam Cmax and AUC were 20% higher in women (N=11) compared to men (N=12). However, clearances adjusted for body weight were comparable.

Race

Formal pharmacokinetic studies of the effects of race have not been conducted. Cross study comparisons involving Caucasians (N=12) and Asians (N=12), however, show that pharmacokinetics of levetiracetam were comparable between the two races. Because levetiracetam is primarily renally excreted and there are no important racial differences in creatinine clearance, pharmacokinetic differences due to race are not expected.

Renal Impairment

The disposition of levetiracetam was studied in adult subjects with varying degrees of renal function. Total body clearance of levetiracetam is reduced in patients with impaired renal function by 40% in the mild group (CLcr = 50 to 80 mL/min), 50% in the moderate group (CLcr = 30 to 50 mL/min) and 60% in the severe renal impairment group (CLcr <30 mL/min). Clearance of levetiracetam is correlated with creatinine clearance.

In anuric (end stage renal disease) patients, the total body clearance decreased 70% compared to normal subjects (CLcr >80 mL/min).

Approximately 50% of the pool of levetiracetam in the body is removed during a standard 4- hour hemodialysis procedure.

Dosage should be reduced in patients with impaired renal function receiving levetiracetam, and supplemental doses should be given to patients after dialysis[see Dosage and Administration (2.5)].

Hepatic Impairment

In subjects with mild (Child-Pugh A) to moderate (Child-Pugh B) hepatic impairment, the pharmacokinetics of levetiracetam were unchanged. In patients with severe hepatic impairment (Child-Pugh C), total body clearance was 50% that of normal subjects, but decreased renal clearance accounted for most of the decrease. No dose adjustment is needed for patients with hepatic impairment.

Drug Interactions:

In vitro data on metabolic interactions indicate that levetiracetam is unlikely to produce, or be subject to, pharmacokinetic interactions.

Levetiracetam and its major metabolite, at concentrations well above Cmax levels achieved within the therapeutic dose range, are neither inhibitors of, nor high affinity substrates for, human liver cytochrome P450 isoforms, epoxide hydrolase or UDP-glucuronidation enzymes. In addition, levetiracetam does not affect the in vitroglucuronidation of valproic acid.

Potential pharmacokinetic interactions of or with levetiracetam were assessed in clinical pharmacokinetic studies (phenytoin, valproate, warfarin, digoxin, oral contraceptive, probenecid) and through pharmacokinetic screening in the placebo-controlled clinical studies in epilepsy patients.

Phenytoin

Levetiracetam (3000 mg daily) had no effect on the pharmacokinetic disposition of phenytoin in patients with refractory epilepsy. Pharmacokinetics of levetiracetam were also not affected by phenytoin.

Valproate

Levetiracetam (1500 mg twice daily) did not alter the pharmacokinetics of valproate in healthy volunteers. Valproate 500 mg twice daily did not modify the rate or extent of levetiracetam absorption or its plasma clearance or urinary excretion. There also was no effect on exposure to and the excretion of the primary metabolite, ucb L057.

Other Antiepileptic Drugs

Potential drug interactions between levetiracetam and other AEDs (carbamazepine, gabapentin, lamotrigine, phenobarbital, phenytoin, primidone and valproate) were also assessed by evaluating the serum concentrations of levetiracetam and these AEDs during placebo-controlled clinical studies. These data indicate that levetiracetam does not influence the plasma concentration of other AEDs and that these AEDs do not influence the pharmacokinetics of levetiracetam.

Effect Of AEDs In Pediatric Patients

There was about a 22% increase of apparent total body clearance of levetiracetam when it was co-administered with enzyme-inducing AEDs. Dose adjustment is not recommended. Levetiracetam had no effect on plasma concentrations of carbamazepine, valproate, topiramate, or lamotrigine.

Oral Contraceptives

Levetiracetam (500 mg twice daily) did not influence the pharmacokinetics of an oral contraceptive containing 0.03 mg ethinyl estradiol and 0.15 mg levonorgestrel, or of the luteinizing hormone and progesterone levels, indicating that impairment of contraceptive efficacy is unlikely. Coadministration of this oral contraceptive did not influence the pharmacokinetics of levetiracetam.

Digoxin

Levetiracetam (1000 mg twice daily) did not influence the pharmacokinetics and pharmacodynamics (ECG) of digoxin given as a 0.25 mg dose every day. Coadministration of digoxin did not influence the pharmacokinetics of levetiracetam.

Warfarin

Levetiracetam (1000 mg twice daily) did not influence the pharmacokinetics of R and S warfarin. Prothrombin time was not affected by levetiracetam. Coadministration of warfarin did not affect the pharmacokinetics of levetiracetam.

Probenecid

Probenecid, a renal tubular secretion blocking agent, administered at a dose of 500 mg four times a day, did not change the pharmacokinetics of levetiracetam 1000 mg twice daily. Css max of the metabolite, ucb L057, was approximately doubled in the presence of probenecid while the fraction of drug excreted unchanged in the urine remained the same. Renal clearance of ucb L057 in the presence of probenecid decreased 60%, probably related to competitive inhibition of tubular secretion of ucb L057. The effect of levetiracetam on probenecid was not studied.

13 NONCLINICAL TOXICOLOGY

13.1 Carcinogenesis, Mutagenesis, Impairment Of Fertility

Carcinogenesis

Rats were dosed with levetiracetam in the diet for 104 weeks at doses of 50, 300 and 1800 mg/kg/day. The highest dose is 6 times the maximum recommended daily human dose (MRHD) of 3000 mg on a mg/m^2 basis and it also provided systemic exposure (AUC) approximately 6 times that achieved in humans receiving the MRHD. There was no evidence of carcinogenicity. In mice, oral administration of levetiracetam for 80 weeks (doses up to 960 mg/kg/day) or 2 years (doses up to 4000 mg/kg/day, lowered to 3000 mg/kg/day after 45 weeks due to intolerability) was not associated with an increase in tumors. The highest dose tested in mice for 2 years (3000 mg/kg/day) is approximately 5 times the MRHD on a mg/m^2 basis.

Mutagenesis

Levetiracetam was not mutagenic in the Ames test or in mammalian cells in vitro in the Chinese hamster ovary/HGPRT locus assay. It was not clastogenic in an in vitroanalysis of metaphase chromosomes obtained from Chinese hamster ovary cells or in an in vivomouse micronucleus assay. The hydrolysis product and major human metabolite of levetiracetam (ucb L057) was not mutagenic in the Ames test or the in vitromouse lymphoma assay.

Impairment Of Fertility

No adverse effects on male or female fertility or reproductive performance were observed in rats at oral doses up to 1800 mg/kg/day (6 times the maximum recommended human dose on a mg/m^2 or systemic exposure [AUC] basis).

14 CLINICAL STUDIES

In the following studies, statistical significance versus placebo indicates a p value <0.05.

14.1 Partial Onset Seizures

Effectiveness In Partial Onset Seizures In Adults With Epilepsy

The effectiveness of levetiracetam as adjunctive therapy (added to other antiepileptic drugs) in adults was established in three multicenter, randomized, double-blind, placebo-controlled clinical studies in patients who had refractory partial onset seizures with or without secondary generalization. The tablet formulation was used in all these studies. In these studies, 904 patients were randomized to placebo, 1000 mg, 2000 mg, or 3000 mg/day. Patients enrolled in Study 1 or Study 2 had refractory partial onset seizures for at least two years and had taken two or more classical AEDs. Patients enrolled in Study 3 had refractory partial onset seizures for at least 1 year and had taken one classical AED. At the time of the study, patients were taking a stable dose regimen of at least one and could take a maximum of two AEDs. During the baseline period, patients had to have experienced at least two partial onset seizures during each 4-week period.

Study 1

Study 1 was a double-blind, placebo-controlled, parallel-group study conducted at 41 sites in the United States comparing levetiracetam 1000 mg/day (N=97), levetiracetam 3000 mg/day (N=101), and placebo (N=95) given in equally divided doses twice daily. After a prospective baseline period of 12 weeks, patients were randomized to one of the three treatment groups described above. The 18-week treatment period consisted of a 6-week titration period, followed by a 12-week fixed dose evaluation period, during which concomitant AED regimens were held constant. The primary measure of effectiveness was a between group comparison of the percent reduction in weekly partial seizure frequency relative to placebo over the entire randomized treatment period (titration +evaluation period). Secondary outcome variables included the responder rate (incidence of patients with ≥50% reduction from baseline in partial onset seizure frequency). The results of the analysis of Study 1 are displayed in Table 10.

Table 10: Reduction In Mean Over Placebo In Weekly Frequency Of Partial Onset Seizures In Study 1
 | Placebo (N=95) | Levetiracetam 1000 mg/day (N=97) | Levetiracetam 3000 mg/day (N=101)
Percent reduction in partial seizure frequency over placebo | ___ | 26.1%* | 30.1%*
* statistically significant versus placebo

The percentage of patients (y-axis) who achieved ≥50% reduction in weekly seizure rates from baseline in partial onset seizure frequency over the entire randomized treatment period (titration + evaluation period) within the three treatment groups (x-axis) is presented in Figure 1.

Figure 1: Responder Rate (≥50% Reduction From Baseline) In Study 1

*statistically significant versus placebo

Study 2

Study 2 was a double-blind, placebo-controlled, crossover study conducted at 62 centers in Europe comparing levetiracetam 1000 mg/day (N=106), levetiracetam 2000 mg/day (N=105), and placebo (N=111) given in equally divided doses twice daily.

The first period of the study (Period A) was designed to be analyzed as a parallel-group study. After a prospective baseline period of up to 12 weeks, patients were randomized to one of the three treatment groups described above. The 16-week treatment period consisted of the 4-week titration period followed by a 12-week fixed dose evaluation period, during which concomitant AED regimens were held constant. The primary measure of effectiveness was a between group comparison of the percent reduction in weekly partial seizure frequency relative to placebo over the entire randomized treatment period (titration + evaluation period). Secondary outcome variables included the responder rate (incidence of patients with ≥50% reduction from baseline in partial onset seizure frequency). The results of the analysis of Period A are displayed in Table 11.

Table 11: Reduction In Mean Over Placebo In Weekly Frequency Of Partial Onset Seizures In Study 2: Period A
 | Placebo (N=111) | Levetiracetam 1000 mg/day (N=106) | Levetiracetam 2000 mg/day (N=105)
Percent reduction in partial seizure frequency over placebo | ___ | 17.1%* | 21.4%*
* statistically significant versus placebo

The percentage of patients (y-axis) who achieved ≥50% reduction in weekly seizure rates from baseline in partial onset seizure frequency over the entire randomized treatment period (titration + evaluation period) within the three treatment groups (x-axis) is presented in Figure 2.

Figure 2: Responder Rate (≥50% Reduction From Baseline) In Study 2: Period A

*statistically significant versus placebo

The comparison of levetiracetam 2000 mg/day to levetiracetam 1000 mg/day for responder rate was statistically significant (P=0.02). Analysis of the trial as a cross-over yielded similar results.

Study 3

Study 3 was a double-blind, placebo-controlled, parallel-group study conducted at 47 centers in Europe comparing levetiracetam 3000 mg/day (N=180) and placebo (N=104) in patients with refractory partial onset seizures, with or without secondary generalization, receiving only one concomitant AED. Study drug was given in two divided doses. After a prospective baseline period of 12 weeks, patients were randomized to one of two treatment groups described above. The 16-week treatment period consisted of a 4-week titration period, followed by a 12-week fixed dose evaluation period, during which concomitant AED doses were held constant. The primary measure of effectiveness was a between group comparison of the percent reduction in weekly seizure frequency relative to placebo over the entire randomized treatment period (titration + evaluation period). Secondary outcome variables included the responder rate (incidence of patients with ≥50% reduction from baseline in partial onset seizure frequency). Table 12 displays the results of the analysis of Study 3.

Table 12: Reduction In Mean Over Placebo In Weekly Frequency Of Partial Onset Seizures In Study 3
 | Placebo (N=104) | Levetiracetam 3000 mg/day (N=180)
Percent reduction in partial seizure frequency over placebo | – | 23.0%*
* statistically significant versus placebo

The percentage of patients (y-axis) who achieved ≥50% reduction in weekly seizure rates from baseline in partial onset seizure frequency over the entire randomized treatment period (titration + evaluation period) within the two treatment groups (x-axis) is presented in Figure 3.

Figure 3: Responder Rate (≥50% Reduction From Baseline) In Study 3

*statistically significant versus placebo
Effectiveness In Partial Onset Seizures In Pediatric Patients 4 Years To 16 Years With Epilepsy

The effectiveness of levetiracetam as adjunctive therapy (added to other antiepileptic drugs) in pediatric patients was established in one multicenter, randomized double-blind, placebo-controlled study, conducted at 60 sites in North America, in children 4 to 16 years of age with partial seizures uncontrolled by standard antiepileptic drugs (AEDs). Eligible patients on a stable dose of 1 to 2 AEDs, who still experienced at least 4 partial onset seizures during the 4 weeks prior to screening, as well as at least 4 partial onset seizures in each of the two 4-week baseline periods, were randomized to receive either levetiracetam or placebo. The enrolled population included 198 patients (levetiracetam N=101, placebo N=97) with refractory partial onset seizures, whether or not secondarily generalized. The study consisted of an 8-week baseline period and 4-week titration period followed by a 10week evaluation period. Dosing was initiated at a dose of 20 mg/kg/day in two divided doses. During the treatment period, levetiracetam doses were adjusted in 20 mg/kg/day increments, at 2-week intervals to the target dose of 60 mg/kg/day. The primary measure of effectiveness was a between group comparison of the percent reduction in weekly partial seizure frequency relative to placebo over the entire 14-week randomized treatment period (titration + evaluation period). Secondary outcome variables included the responder rate (incidence of patients with ≥50% reduction from baseline in partial onset seizure frequency per week). Table 13 displays the results of this study.

Table 13: Reduction In Mean Over Placebo In Weekly Frequency Of Partial Onset Seizures
 | Placebo (N=97) | Levetiracetam (N=101)
Percent reduction in partial seizure frequency over placebo | - | 26.8%*
* statistically significant versus placebo

The percentage of patients (y-axis) who achieved ≥50% reduction in weekly seizure rates from baseline in partial onset seizure frequency over the entire randomized treatment period (titration + evaluation period) within the two treatment groups (x-axis) is presented in Figure 4.

Figure 4: Responder Rate (≥ 50% Reduction From Baseline)

Clinical trial information in pediatric patients less than 4 years of age as adjunctive therapy in the treatment of partial onset seizures is approved for UCB, Inc.'s levetiracetam tablets and oral solution. However, due to UCB, Inc.'s marketing exclusivity rights, this drug product is not labeled with that pediatric information.

14.2 Myoclonic Seizures In Patients With Juvenile Myoclonic Epilepsy

Effective ne ss Of My ocl onic Sei z u res In Patie nts ≥12 Ye a rs Of Age With J uve nile My ocl o nic Epile p sy (JM E)

The e ffecti ve ne ss of le veti rac etam as a dj uncti ve t he r a py (a d ded to ot h er a ntie pile ptic d rug s) in patie nts 12 yea rs of a ge a nd ol der with j uve nile m y ocl onic e pile p sy (J ME) e xpe ri e nci ng m yocl o nic seiz ures was e sta bl i s hed in o ne multice nte r, r a ndomiz e d, do ubl e-bli n d, place bo-c o nt rolled st u d y, c on ducted at 37 sites in 14 c o unt r ie s. Of t he 120 patie nts e n r olle d, 1 13 had a dia g no sis of c o n fi rmed or s u s pected J ME. Eli gi ble patie nts on a sta ble do se of 1 a ntie pile ptic drug (A ED) e x pe rie n ci ng one or m ore m yocl o nic sei zures per d ay for at lea st 8 d a ys duri ng t he p ro s pecti ve 8-week ba seli ne p e ri od we re r a nd o mized to eit h er le veti racetam or place bo (le veti racetam N= 60, place bo N= 6 0). Patie nts we re tit rated over 4 wee ks to a ta rget do se of 3 000 mg/ day a nd t reated at a sta ble do se of 3000 mg/ d ay over 12 wee ks (e va l uati on p eri od). St u dy d r ug was gi v en in 2 di vi d ed do se s.

The pri ma ry mea s ure of e f fec ti ve ne ss was t he prop o rti on of patie nts with at lea st 50% re ducti on in t he nu m ber of d a ys per we ek with one or more myoc l onic sei zu res duri ng t he t reat me nt p e ri od (tit rati on + e val uati on pe r i od s) as c ompa red to ba seli ne. T a ble 14 di s pla ys t he re s ults for t he 113 patie nts with JME in t his st udy.

Ta ble 14: Re s pond er Rate (≥ 5 0% Re ducti on F rom Ba seli ne) In M yoc l onic Seiz ure Da ys Per Week for Patie nts with J ME

 | Pl acebo (N = 59) | Le ve tir ace tam (N = 54)
Pe rce nta ge of re s po n de rs | 23.7% | 60.4%*

* stati stica lly si gni fica nt ve r sus place bo

14.3 Primary Generalized Tonic-Clonic Seizures

Effective ne ss In P rim a ry Ge n e r ali zed T onic - Cl onic Sei z u res In Patie nts ≥6 Ye a rs Of Age

The e ffecti ve ne ss of le veti rac etam as a dj uncti ve t he r a py (a d ded to ot h er a ntie pile ptic d rug s) in patie nts 6 ye a rs of a ge a nd ol der with i di opat hic g e ne ralized e pile p sy e xpe ri e nci ng pri ma ry ge n e r alized t onic -cl onic (PG T C) sei z ures was e sta bli s hed in one m ultice nte r, ra ndomiz e d, d ouble - bli nd, pl ace bo-c o nt rolled st u d y, c o ndu cted at 50 sites in 8 c o unt rie s. Eli gi ble patie nts on a sta ble d o se of 1 or 2 a ntie pile ptic dr u gs (A ED s) e x pe rie nci ng at lea st 3 PG TC seiz ures duri ng t he 8 -week c om bi ned ba seli ne pe r i od (at lea st o ne PG TC seiz ure duri ng t he 4 wee ks pr i or to t he pro s pecti ve ba seli ne pe ri od a nd at lea st one PG TC seiz ure duri ng t he 4 -week p r os pecti ve ba seli ne pe ri od) we re ra n dom ized to eit her le veti racetam or place bo. T he 8-we ek c o m bi n ed ba seli ne pe ri od is re fe rr ed to as " ba seli ne" in t he re mai n der of t his secti on. The po p ulati on i ncl u ded 164 patie nts (le veti racetam N= 8 0, place bo N= 84) with i di opa t hic ge ne ralized e pile p sy (pr e domi nately j uve nile myocl onic e pile p s y, j uv e n ile a b se nce e pile p s y, c hil d ho od a b se nce e pile p s y, or e pile p sy with G ra nd Mal seiz ures on awa ke ni n g) e xpe rie nci ng pri m a ry g e ne rali zed t onic -cl o nic seiz ure s. Each of t he se s ynd r omes of i di opa t hic ge ne ralized e pil e p sy was well re pre se nted in t his patie nt p op ulati on. Patie nts we re tit rated over 4 wee ks to a ta rget do se of 3 0 00 mg/ day f or a dults or a pe diat r ic ta rget do se of 60 mg/ k g/ day a nd t reated at a sta ble do se of 3000 mg/ d ay (or 60 mg/ kg / d ay for c hil dre n) over 20 wee ks (e va l uati on pe r i od). St udy drug was gi ven in 2 e qually di vi ded d o ses per da y.

The pri ma ry mea s ure of e f fec ti ve ne ss was t he pe rce nt re d ucti on fr om ba seli ne in wee k ly PG TC seiz ure fre que n cy f or le veti racetam a nd place bo t reat me nt gr o ups over t he t reat me nt p e ri od (tit r ati on + e val uati on pe ri o d s). T he re was a stati stic ally si gni fica nt dec rea se from ba seli ne in PG TC fre qu e ncy in t he le veti raceta m-t reat ed patie nts c omp a red to t he pl ace bo-t reated patie nt s.

Ta ble 15: Me di an Pe rce nt Re d ucti on F rom Ba seli ne In PG TC Seiz ure F re que ncy Per We ek

 | Pl acebo (N = 84) | Le ve tir ace tam (N = 78)
Pe rce nt re ducti on in PG TC seiz ure fre qu e ncy | 44.6% | 77.6%*

* stati stica lly si gni fica nt ve r sus place bo

The pe rc e nta ge of patie nts (y -a xi s) w ho ac hie v ed ≥ 5 0% re d ucti on in wee k ly seiz ure rates from ba seli ne in PG TC seiz ure fre qu e ncy over t he e nti re ra n domiz ed t r eat me nt pe ri od (tit rati on + e va l uati on pe r i od) wit hin t he two t reat me nt g r oups (x-a xi s) is pr e se nted in Fi gure 6.

Fi gure 6: Re s ponder Rate (≥ 5 0% Re ducti on F rom Ba seli ne) In PG TC Seiz ure F re que n cy Per Week
*statistically significant versus placebo

16 HOW SUPPLIED/STORAGE AND HANDLING

16.1 How Supplied

Levetiracetam Oral Solution, USP 1 00 mg/ mL is a clea r, c ol o rle ss, gra p e -fla v o red li qu i d. It is su pplied in 16 fl. oz. (473 mL) w hite HDPE bottles (NDC 62332 -626 -16).

16.2 Storage

St ore at 20° to 2 5°C (68° to 7 7°F) ; e x c ur si ons pe rmitted to 15° to 30°C (59° to 86°F) [ see USP C ont rolled R oom Te mpe rat u re ].

Dispense in a tight, light-resistant container with a child-resistant closure.

Di s pe n se acc ompa nyi ng Me d icati on G ui de to ea ch patie nt.

17 PATIENT COUNSELING INFORMATION

See FDA-approved Patient Labeling (Medication Guide).

Counsel patients on the benefits and risks of receiving levetiracetam. Provide the Medication Guide to patients and/or caregivers, and instruct them to read the Medication Guide prior to taking levetiracetam. Instruct patients to take levetiracetam only as prescribed.

Suicidal Behavior and Ideation

Counsel patients, their caregivers, and/or families that antiepileptic drugs (AEDs), including levetiracetam, may increase the risk of suicidal thoughts and behavior and advise patients to be alert for the emergence or worsening of symptoms of depression; unusual changes in mood or behavior; or suicidal thoughts, behavior, or thoughts about self-harm. Advise patients, their caregivers, and/or families to immediately report behaviors of concern to a healthcare provider.

Psychiatric Reactions and Changes in Behavior

Advise patients that levetiracetam may cause changes in behavior (e.g. aggression, agitation, anger, anxiety, apathy, depression, hostility, and irritability) and in rare cases, psychotic symptoms have occurred.

Effects on Driving or Operating Machinery

Inform patients that levetiracetam may cause dizziness and somnolence. Inform patients not to drive or operate machinery until they have gained sufficient experience on levetiracetam to gauge whether it adversely affects their ability to drive or operate machinery.

Anaphylaxis and Angioedema
Advise patients to discontinue Levetiracetam and seek medical care if they develop signs and symptoms of anaphylaxis or
angioedema [see Warnings and Precautions (5.4)].

Dermatological Adverse Reactions

Advise patients that serious dermatological adverse reactions have occurred in patients treated with levetiracetam and instruct them to call their physician immediately if a rash develops.
Pregnancy
Advise patients to notify their healthcare provider if they become pregnant or intend to become pregnant during levetiracetam therapy. Encourage patients to enroll in the North American Antiepileptic Drug (NAAED) pregnancy registry if they become pregnant. This registry is collecting information about the safety of antiepileptic drugs during pregnancy. To enroll, patients can call the toll free number 1-888-233-2334 [see Use In Specific Populations (8.1)].

Manufactured by:
Lannett Company, Inc.
Carmel, NY 10512
Manufactured for:

Alembic Pharmaceuticals, Inc.
750 Route 202, Bridgewater, NJ 08807
USA

Rev. 09/19

MEDICATION GUIDE

Levetiracetam Oral Solution, USP

Read t his Me dicati on G ui de be fore y ou sta rt ta ki ng Levetiracetam Oral Solution, USP a nd ea ch ti me you get a r e fill. The re m ay be new i nformati o n. This i n f ormati on does not ta ke t he place of tal k i ng to y our healt hca re pr o vi der a bout your me dical c o nditi on or t reat me nt.

Wh at is the m o st imp or tant in form ati on I sh ould kn ow ab out Levetiracetam Oral Solution, USP?

Like other an tiepilep tic dr u g s, Levetiracetam Oral Solution, USP m ay c au se suicid al th ou g h ts or ac ti ons in a very sm all number of pe ople, ab out 1 in 500 pe ople taking i t.

C all a he al thc are pr ovider r i ght aw ay if you h ave any of the se s ymp to m s, e speci ally if they are new, w or se, or w or ry you:

• t houghts a b out s uici de or d yi ng

• atte mpts to c ommit s uici de

• new or w or se de pre ssi on

• new or w or se a nxiety

• feeli ng a gitated or re stle ss

• pa nic attac ks

• t rouble slee pi ng (i n s omnia)

• new or w or se i r rita bility

• acti ng a ggre ssi ve, be i ng a n g r y, or vi ole nt

• acti ng on da ng e rous i m p ul ses

• an e xt re me i n c rea se in acti v ity a nd tal ki ng (m a nia)

• ot her u nu s ual c h a nges in b e ha vi or or m o od

Do n ot s top Levetiracetam Oral Solution, USP wi th out fir st talking to a he al thc are pr ovide r.

• St oppi ng Levetiracetam Oral Solution, USP s udde n ly can c a u se se ri ous pr o ble m s. St oppi ng a seiz ure me dici ne su dde n ly can c a u se seiz ures t hat will not st op (stat us e pile ptic u s).

• S uici dal t hou g hts or acti ons can be ca u sed by t h i ngs ot her t han me dici ne s. If y ou h a ve suici dal t hou g hts or acti on s, y o ur healt hca re provi d er may c heck for ot her ca u se s.

How c an I w atch for e arly symp toms of suic id al th ou gh ts and ac ti on s?

• Pay atte nti on to a ny c h a nge s, e s pecially s udden c ha nge s, in mo o d, b e ha vi or s, t h ou g ht s, or feeli ng s.

• Keep all foll ow - up vi sits wi th yo ur healt hc a re p r ovi der as sc he dule d.

• Call your healt hca re pr o vi d er between vi sits as nee de d, e specially if you a re w o r ried a bo ut s ympt om s.

Wh at is Levetiracetam Oral Solution, USP?

Levetiracetam Oral Solution, USPis a pre sc ri pti on m e dici ne ta k en by m o uth t hat is u sed with ot her me dici nes to t reat:

• pa rtial on set seiz ures in pe ople 4 years of a ge a nd ol d er with e pile p sy

• myocl onic seiz ures in pe ople 12 ye a rs of a ge a nd ol der wi th j uve nile m yocl o nic e pile p sy

• pri ma ry ge ne ralized t oni c-c l onic seiz ures in pe o ple 6 yea rs of a ge a nd ol der with ce rtain t ypes of g e ne ralized e pile p s y.

It is not kno wn if Levetiracetam Oral Solution, USP is sa fe or e ffe cti ve in c hil dren u n der 1 mon th of a ge.

Be fore ta ki ng yo ur me dici ne, ma ke s ure y ou ha ve recei v ed t he c orrect me dici ne. C o m pa re t he na me a bove with t he na me on y our bottle a nd t he a ppea ra nce of y our m e dici ne with t he de sc ri p ti on of Levetiracetam Oral Solution, USP p r ovi d ed bel ow. Tell yo ur pha rmaci st i mme diately if y ou t hi nk y ou ha ve be en gi v en t he w r o ng m e dici ne.

Levetiracetam Oral Solution, USPis a clea r, c ol orle ss, gr a pe -fla v o red li qui d.

Who should not take Levetiracetam Oral solution ?

Do not take Levetiracetam oral solution if you are allergic to levetiracetam.

Wh at sh ould I tell my he al thc are pr ovider be fore s tar ti ng Levetiracetam Oral Solution, USP?

Be fore ta ki ng Levetiracetam Oral Solution, USP, tell yo ur healt hc are prov i der a b out all of y o ur me dical c onditi on s, i nc l udi ng if you:

• ha ve or ha ve had de pre ssi on, mood pr o ble ms or s uici dal t h oughts or be h a vi or

• ha ve ki d ney proble ms

• a re pre g na nt or pla n ni ng to bec ome pr e gna nt. It is not k n own if Levetiracetam Oral Solution, USP will ha rm yo ur u n bo rn ba b y. Y ou a nd your healt hca re prov i der will ha ve to deci de if y ou sh ould t a ke Levetiracetam Oral Solution, USP w hile you a re pr e gna nt. If y ou bec ome pre gn a nt w hile ta ki ng Levetiracetam Oral Solution, USP, talk to yo ur healt hca re pr o vi der a bout re gi ste ri ng with t he N orth A m e rican A ntie pile ptic D rug P re g na ncy Re gi st ry. Y ou can e n roll in t h is re gi st ry by calli ng 1- 8 88 - 2 3 3-2 3 34. T he p u rpo se of t his r e gi st ry is to c ollect i nformati on a b o ut t he sa fety of Levetiracetam Oral Solution, USP a nd ot her a ntie pile ptic me dici ne dur i ng p re gn a nc y.

• a re brea st fee di n g. Levetiracetam c an pa ss i n to yo ur milk a nd m ay ha rm y o ur ba b y. Y ou a nd y o ur healt h ca re pr o vi der s hould di sc u ss w het her y ou sh ould ta ke Levetiracetam Oral Solution, USP or brea st -fee d; you sh o uld not do bo t h.

Tell your healt hca re prov i der a bout all t he m e dici nes y ou t a ke, i ncl ud i ng p re sc ri pti on a nd non p re sc ri pti on m e dici ne s, vi ta mi n s, a nd he rbal s uppl e me nt s. Do n ot sta rt a new me dici ne wit h out fi r st tal ki ng with yo ur healt hca re prov i de r.

K now t he me dici nes y ou ta k e. Keep a li st of t hem to s how y our healt hc a re p r ovi d er a nd p ha rmaci st each ti me you get a new me dici ne.

How sh ould I take Levetiracetam Oral Solution, USP?

Ta ke Levetiracetam Oral Solution, USP e xactly as p re sc ri be d.

• Y our healt hc a re p r ovi der will tell you h ow much Levetiracetam Oral Solution, USP to ta ke a nd w hen to ta ke it. Levetiracetam Oral Solution, USP is u s ually ta ken twice a da y. Ta ke Levetiracetam Oral Solution, USP at t he sa me ti mes each d a y.

• Y our healt hc a re p r ovi der m ay c ha n ge y o ur d o se. Do n ot c ha nge y our do se wit hout tal ki ng to y o ur healt hca re p rovi d e r.

• Ta ke Levetiracetam Oral Solution, USP with or wit h out f o od.

• If y o ur healt hc a re p r ovi d er has pre sc ri bed Levetiracetam Oral Solution, USP, be s ure to a sk y our pha rmaci st f or a me dici ne dr o pper or me dici ne c up to help y ou me a s ure t he c o r rect a mo u nt of Levetiracetam Oral Solution, USP. Do n ot u se a h o u se hold tea s p o on. A sk your pha rmaci st for i n st ructi ons on how to u se t he mea s uri ng de v ice t he ri ght wa y.

• If y ou mi ss a do se of Levetiracetam Oral Solution, USP, ta ke it as s oon as you re me m be r. If it is al mo st ti me for y our ne xt d o s e, j u st s kip t he mi ssed do se. Ta ke t he ne xt dose at your r e gular ti me. Do n ot take two d o ses at the s ame time.

• If y ou ta ke t oo mu ch Levetiracetam Oral Solution, USP, call yo ur l ocal P oi s on C ont rol Ce nter or go to t he nea re st e me rg e ncy r oom ri g ht awa y.

Wh at sh ould I avoid while taking Levetiracetam Oral Solution, USP?

Do not d ri ve, o pe rate ma c hi n e ry or do ot her da nge r ous acti vities until you k n ow how Levetiracetam Oral Solution, USP a ffects you. Levetiracetam Oral Solution, USP may ma ke you dizzy or slee py.

Wh at are the p o ssible s ide e ffec ts of Levetiracetam Oral Solution, USP?

See “ W hat is t he mo st i mporta nt i nfo r mati on I sh ould know a bout Levetiracetam Oral Solution, USP?”

Levetiracetam Oral Solution, USPc an ca u se se ri ous si de e ffect s.

Call your healt hca re pr o vi der ri ght away if you ha ve a ny of t he se s ympt om s:

• mood a nd b e ha vi or c ha n ges s uch as a ggre ssi on, a gitati o n, a nge r, a nxiet y, a pat hy, mo od swi ng s, de pre ssi on, h o stilit y, a nd i rrita bilit y. A few pe ople m ay get p s yc ho tic s ympt oms s uch as hall uci n ati ons (seei ng or hea ri ng t hi ngs t hat a re really not t he r e), del usi ons (fal se or st ra nge t h ou g hts or belie f s) a nd u n u s ual be h a vi or.

• e xt re me slee pi ne ss, ti re dne ss, a nd wea k ne ss

• proble ms with mu scle c o ord i nati on (p roble ms wal ki ng a nd movi n g)

• allergic reactions such as swelling of the face, lips, eyes, tongue, and throat, trouble

swallowing or breathing, and hives.

• a s kin ra s h. Se ri ous s kin ra s hes can ha pp en a fter you sta rt ta ki ng Levetiracetam Oral Solution, USP. Th e re is no way to tell if a mild ra sh will bec ome a se ri ous reacti o n.

The mo st c om m on si de e f fects seen in pe o ple w ho ta ke Levetiracetam Oral Solution, USP i ncl ude:

• slee pi ne ss

• wea kne ss

• i nfecti on

• dizzi ne ss

The mo st c om m on si de e f fects seen in c hil dr en w ho t a ke Levetiracetam Oral Solution, USP i ncl u de, in a dditi on to t h o se li sted a bove:

• ti re dne ss

• acti ng a ggre ssi ve

• na sal c onge sti on

• dec rea sed a ppetite

• i rrita bility

The se si de e ffects can ha p pen at a ny ti me b ut ha p pen m ore o ften wit hin t he fi r st 4 wee ks of t reat me nt e xce pt for i nfecti o n.

Tell your healt hca re prov i der if you ha ve a ny si de e f fect t hat bot he rs y ou or t hat d oes not go awa y.

The se a re not all t he po ssi ble si de e ffects of Levetiracetam Oral Solution, USP. F or m ore i n forma ti on, a sk y our healt hca re p rov i der or pha rmaci st.

C all your d oc tor f or medic al ad vice ab out side e ffec t s. Y ou m ay rep ort side e ffec ts to FDA at 1 - 800 - FDA -10 8 8.

How sh ould I s tore Levetiracetam Oral Solution, USP?

• St ore Levetiracetam Oral Solution, USP at ro om te mpe ra t ure, 59 °F to 86°F (15°C to 30° C) aw ay from heat a nd li ght.

• Keep Levetiracetam Oral Solution, USP and all medic ines out of the re ach of children.

Gener al in form ati on ab out Levetiracetam OralSolution, USP.

Me dici nes a re s ometi mes pre sc ri bed f or p urpo ses ot h er t han t hose li sted in a Me dicati on G ui de. Do n ot u se Levetiracetam Oral Solution, USP for a c onditi on for w hich it w as not pre sc ri be d. Do n ot gi ve Levetiracetam Oral Solution, USP to ot her pe o ple, e ven if t hey ha ve t he sa me s ympt oms t hat y ou h a ve. It may ha rm t he m.

This Me dicati on G ui de s um ma rizes t he mo st i mporta nt i nf o rmati on a b out Levetiracetam Oral Solution, USP. If y ou w ould li ke more i nformati o n, talk with y our h ealt hca re pr o vi de r. Y ou can a sk your pha r maci st or healt hca re prov i der f or i n f ormati on a b out Levetiracetam Oral Solution, USP t h at is w ritten for health profe ssi onals.

Wh at are the in gredien ts of Levetiracetam Oral Solution, USP?

Levetiracetam Oral Solution, USPacti ve i ngre die nt: l e veti racetam

Inacti ve i n g re die nt s: ace s ul f a me pota ssi um, a rti ficial gr a pe fla vor, cit ric ac i d, gl yc e ri n, maltit ol s ol uti on, met hyl p a ra be n, monoa m moni um gl y c yrrhizi nate, pro p yl pa r a be n, puri fied wate r, s odi um cit rate.

Levetiracetam Oral Solution, USP d oes not c ontain lact o se or gl ut e n. Levetiracetam Oral Solution, USP does c ontain c a rb o hydrate s. T he li quid is dye -fre e.

Information on the use of levetiracetam in pediatric patients less than 4 years of age as adjunctive therapy in the treatment of partial onset seizures is approved for UCB, Inc.’s levetiracetam tablets and oral solution. However, due to UCB, Inc.’s marketing exclusivity rights, this drug product is not labeled with that pediatric information.

Rx Only

This Me dicati on G ui de has b een a pp r oved by t he US F ood a nd D r ug A dmi ni st rati on.

Manufactured by:
Lannett Company, Inc.
Carmel, NY 10512

Manufactured for:

Alembic Pharmaceuticals, Inc.
750 Route 202, Bridgewater, NJ 08807
USA

Re v. 09/19

PACKAGE LABEL.PRINCIPAL DISPLAY PANEL

NDC 62332-626-16
Levetiracetam
Oral Solution, USP
100 mg/mL
Dispense accompanying Medicaton
Guide to each patient.
Rx only
16 fl oz (473 mL)
Alembic